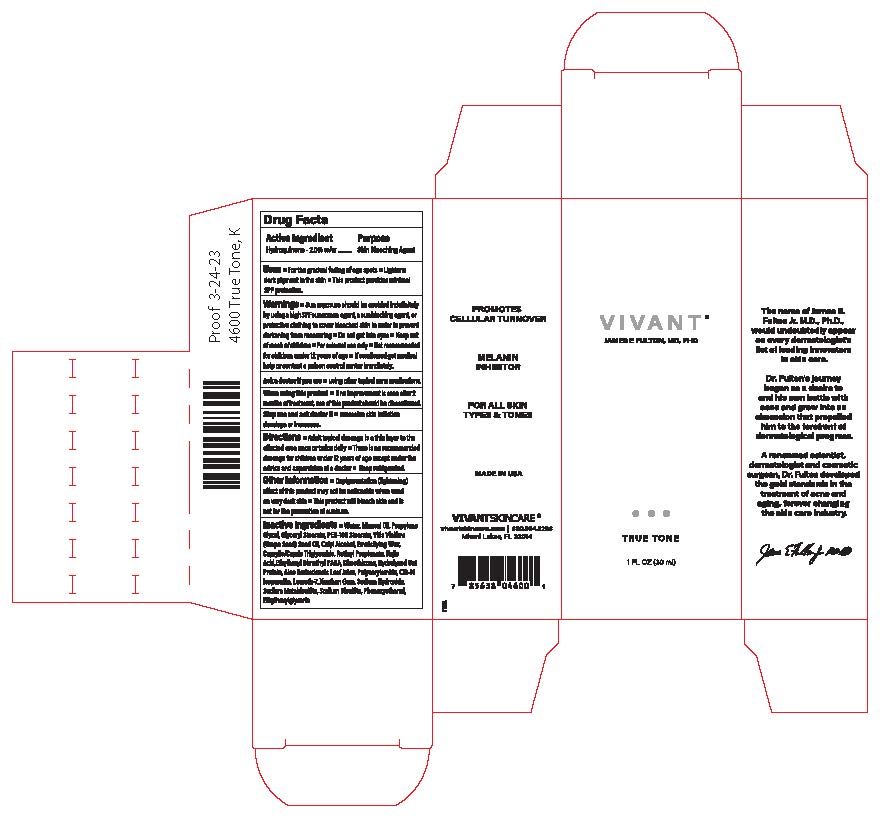 DRUG LABEL: Vivant True Tone
NDC: 63750-002 | Form: CREAM
Manufacturer: Vivant Pharmaceuticals, LLC
Category: otc | Type: HUMAN OTC DRUG LABEL
Date: 20250724

ACTIVE INGREDIENTS: HYDROQUINONE 2 g/100 mL
INACTIVE INGREDIENTS: SODIUM METABISULFITE; PROPYLENE GLYCOL; PADIMATE O; VITIS VINIFERA LEAF OIL; CETYL ALCOHOL; WATER; KOJIC ACID; ALOE VERA LEAF; RETINYL PROPIONATE; MEDIUM-CHAIN TRIGLYCERIDES; AVENA SATIVA LEAF; SODIUM HYDROXIDE; C13-14 ISOPARAFFIN; XANTHAN GUM; CETOSTEARYL ALCOHOL; SODIUM BISULFITE; DIMETHICONE; PHENOXYETHANOL; GLYCERYL 1-STEARATE; PEG-60 STEARATE; POLYSORBATE 60; MINERAL OIL; ETHYLHEXYLGLYCERIN

Vivant True Tone (Export Only)

Active Ingredient

Hydroquinone (2%)

Indication

Skin Bleaching Agent

Uses

■ For the gradual fading of age spots

■ Lightens dark pigment in the skin

■This product provides minimal SPF protection.

Warnings

Warnings ■Sun exposure should be avoided indefinitely by using a high SPF sunscreen agent, a sunblocking agent, or protective clothing to cover bleached skin in order to prevent darkening from reoccurring ■ Do not get into eyes ■Keep out of reach of

children ■For external use only ■Not recommended for children under 12 years of age ■ If swallowed get medical help or contact a poison control center immediately.

Ask a doctor if you are:

using other topical acne medications

Directions

Directions ■ Adult topical dosage is a thin layer to the affected area once or twicedaily■There is no recommended dosage for children under 12 years of age except under the advice and supervision of a doctor ■ Keep refrigerated

Inactive Ingredients

Inactive Ingredients• Water, Mineral Oil, Propylene Glycol, Glyceryl Stearate, PEG-10O Stearate, Vitis Vinifera (Grape Seed) Seed Oil, Cetyl Alcohol, Emulsifying Wax, Caprylic/Capric Triglyceride, Retinyl Propionate, Kojic Acid, EthylhexylDimethyl PABA, Dimethicone, HydrolyzedOat Protein, Aloe Barbadensis Leaf Juice, Polyacrylamide, C13-14 isoparaffin, Laureth-7, Xanthan Gum, Sodium Hydroxide, Sodium Metabisulfite, Sodium Bisullte, Phenoxyethanol, Ethylhexylglycerin

When using this product

if not improvement is seen after 2 months of treatment, use of this products should be discontinued

Stop use and ask the doctor if

excessive skin irritation develops or increases

Warnings

Keep out of reach of children■For external only■Not recommended for children under12 years of age

Other Information

Other Information• Depigmentation(lightening) effect of this product may not be noticeable when used on very dark skin

This product will bleach skin and is not for the prevention of sunburn.